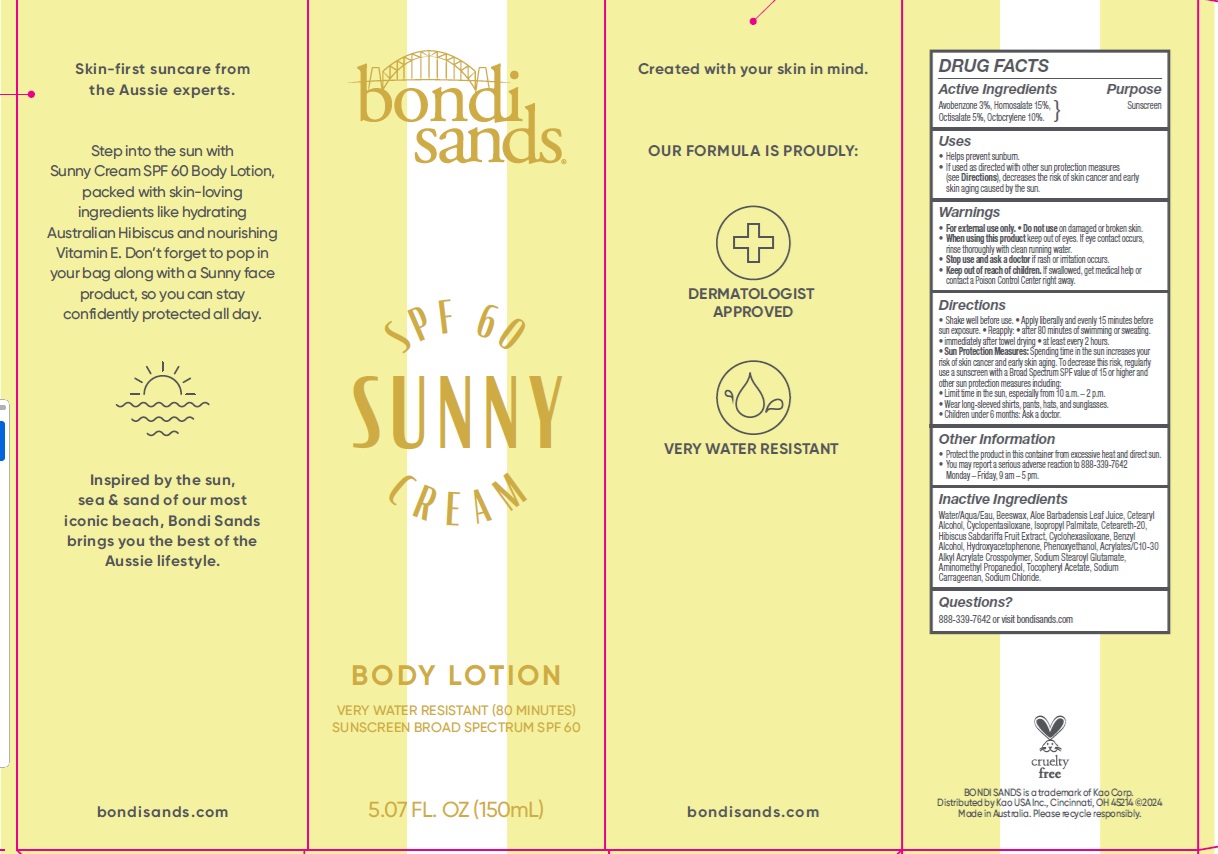 DRUG LABEL: Bondi Sands SPF 60 Sunny Body
NDC: 79950-020 | Form: LOTION
Manufacturer: BONDI SANDS (USA) INC.
Category: otc | Type: HUMAN OTC DRUG LABEL
Date: 20250110

ACTIVE INGREDIENTS: AVOBENZONE 30 mg/1 mL; OCTISALATE 50 mg/1 mL; OCTOCRYLENE 100 mg/1 mL; HOMOSALATE 150 mg/1 mL
INACTIVE INGREDIENTS: ISOPROPYL PALMITATE; AMINOMETHYL PROPANEDIOL; WATER; BEESWAX; CETEARETH-20; .ALPHA.-TOCOPHEROL ACETATE; HYDROXYACETOPHENONE; SODIUM CHLORIDE; BENZYL ALCOHOL; PHENOXYETHANOL; ACRYLATES/C10-30 ALKYL ACRYLATE CROSSPOLYMER (60000 MPA.S); CETEARYL ALCOHOL; CYCLOHEXASILOXANE; SODIUM STEAROYL GLUTAMATE; SODIUM CARRAGEENAN; ALOE VERA LEAF; CYCLOPENTASILOXANE

Bondi Sands SPF 60 Sunny Body Cream

Active Ingredients

Avobenzone 3%

Homosalate 15%

Octisalate 5%

Octocrylene 10%

Purpose

Sunscreen

Uses

- Helps prevent sunburn.
- If used as directed with other sun protection measures (see Directions), decreases the risk of skin cancer and early skin aging caused by the sun.

Warnings

- For external use only

Do not use

on damaged or broken skin.

When using this product

keep out of eyes. If eye contact occurs, rinse thoroughly with clean running water.

Stop use and ask a doctor

if rash or irritation occurs.

Keep out of reach of children.

If swallowed, get medical help or contact a Poison Control Center right away.

Directions

- Shake well before use.
- Apply liberally and evenly 15 minutes before sun exposure.
- Reapply:
- after 80 minutes of swimming or sweating
- immediately after towel drying.
- at least every 2 hours.
- Sun Protection Measures: Spending time in the sun increases your risk of skin cancer and early skin aging. To decrease this risk, regularly use a sunscreen with a Broad Spectrum SPF value of 15 or higher and other sun protection measures including:
- Limit time in the sun, especially from 10 a.m. – 2 p.m.
- Wear long-sleeved shirts, pants, hats, and sunglasses.
- Children under 6 months: Ask a doctor.

Other Information

- Protect the product in this container from excessive heat and direct sun.
- You may report a serious adverse reaction to 888-339-7642; Monday – Friday, 9 am – 5 pm.

Inactive Ingredients

Water/Aqua/Eau, Beeswax, Aloe Barbadensis Leaf Juice, Cetearyl Alcohol, Cyclopentasiloxane, Isopropyl Palmitate, Ceteareth-20, Hibiscus Sabdariffa Fruit Extract, Cyclohexasiloxane, Benzyl Alcohol, Hydroxyacetophenone, Phenoxyethanol, Acrylates/C10-30 Alkyl Acrylate Crosspolymer, Sodium Stearoyl Glutamate, Aminomethyl Propanediol, Tocopheryl Acetate, Sodium Carrageenan, Sodium Chloride.

Questions?

888-339-7642 or visit bondisands.com